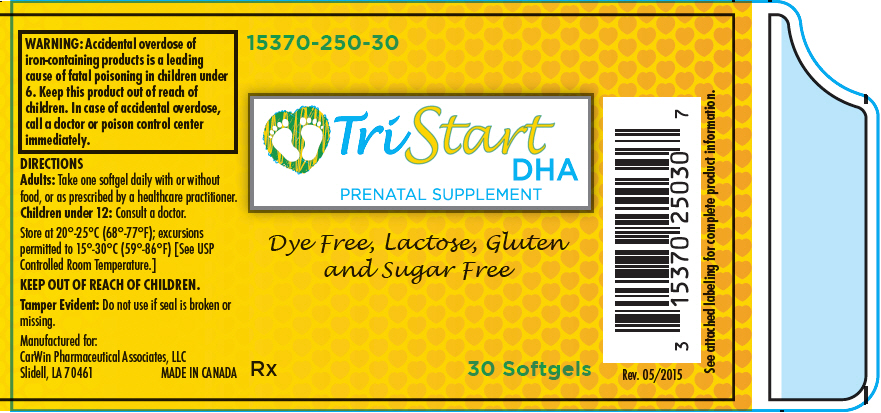 DRUG LABEL: TriStart DHA
NDC: 15370-250 | Form: CAPSULE, LIQUID FILLED
Manufacturer: CarWin Pharmaceutical Associates, LLC
Category: prescription | Type: HUMAN PRESCRIPTION DRUG LABEL
Date: 20240109

ACTIVE INGREDIENTS: ASCORBIC ACID 55 mg/1 1; CHOLECALCIFEROL 1000 [iU]/1 1; .ALPHA.-TOCOPHEROL ACETATE, D- 15 [iU]/1 1; THIAMINE HYDROCHLORIDE 1.3 mg/1 1; RIBOFLAVIN 1.8 mg/1 1; NIACIN 5 mg/1 1; PYRIDOXINE HYDROCHLORIDE 35 mg/1 1; LEVOMEFOLATE MAGNESIUM 600 ug/1 1; FOLIC ACID 400 ug/1 1; CYANOCOBALAMIN 14 ug/1 1; IRON PENTACARBONYL 31 mg/1 1; POTASSIUM IODIDE 200 ug/1 1; MAGNESIUM OXIDE 30 mg/1 1; DOCONEXENT 200 mg/1 1; ICOSAPENT 15 mg/1 1
INACTIVE INGREDIENTS: GELATIN, UNSPECIFIED; GLYCERIN; WATER; YELLOW WAX; CARAMEL; LECITHIN, SOYBEAN; ORANGE; ETHYL VANILLIN

TriStart DHA
PRENATAL SUPPLEMENT

DESCRIPTION

Supplement Facts
Serving Size: 1 Softgel
Servings per container: 30
 | Amount Per Serving | %Daily Value | %Daily Value for Pregnant and Lactating Women
Vitamin C | 55 mg | 92% | 92%
(as ascorbic acid)
Vitamin D3 | 1000 IU | 250% | 250%
(as cholecalciferol)
Vitamin E | 15 IU | 50% | 50%
(as d-alpha-tocopheryl acetate)
Thiamin | 1.3 mg | 87% | 76%
(as thiamine HCl, Vitamin B1)
Riboflavin (Vitamin B2) | 1.8 mg | 106% | 90%
Niacin (as nicotinic acid) | 5 mg | 25% | 25%
Vitamin B6 | 35 mg | 1750% | 1400%
(as pyridoxine HCl)
Folate (as 630 mcg of L-Methylfolate Magnesium, molar equivalent to 600mcg of L-Methylfolic acid; and 400mcg of folic acid) | 1 mg | 250% | 125%
Vitamin B12 | 14 mcg | 233% | 175%
(as cyanocobalamin)
Iron (as carbonyl iron) | 31 mg | 172% | 172%
Iodine | 200 mcg | 133% | 133%
(as Potassium Iodide)
Magnesium | 30 mg | 8% | 7%
(as Magnesium Oxide)
Docosahexaenoic Acid | 200mg | [Daily Values (DV) not established.]
(DHA)
Eicosapentaenoate Acid | 15 mg
(EPA)

OTHER INGREDIENTS: Gelatin (bovine), Glycerin, Purified Water, Yellow Bees Wax, Caramel Powder, Soy Lecithin, Natural Orange Flavor, Ethyl Vanillin.

Contains: Soy and Fish

TriStart DHA™ Softgel capsules are dye free, lactose, gluten and sugar free. They do not contain any artificial flavors or sweeteners. TriStart DHA™ contains bovine gelatin.

INDICATIONS

TriStart DHA™ is an orally administered multivitamin/multimineral fatty acid dietary supplement indicated to improve the nutritional status of women throughout pregnancy and in the postnatal period for both lactating and nonlactating mothers. TriStart DHA™ can also be beneficial in improving the nutritional status of women prior to conception. [This statement has not been evaluated by the Food and Drug Administration. This product is not intended to diagnose, treat, cure, or prevent disease.]

CONTRAINDICATIONS

TriStart DHA™ is contraindicated in patients with a known hypersensitivity to any of the ingredients.

WARNING

Accidental overdose of iron-containing products is a leading cause of fatal poisoning in children under 6. Keep this product out of reach of children. In case of accidental overdose, call a doctor or poison control center immediately.

WARNINGS

Caution is recommended in patients taking anticonvulsant medications as folate may interfere with anticonvulsant medication, and may lower seizure threshold. Furthermore, anticonvulsant medications may interfere with folate metabolism.

PRECAUTIONS

Folic acid alone is improper therapy in the treatment of pernicious anemia and other megaloblastic anemias where Vitamin B12 is deficient. Folic acid in doses above 0.1 mg daily may obscure pernicious anemia in that hematologic remission can occur while neurological manifestations progress.

Ingestion of more than 3 grams of omega-3 fatty acids (such as DHA and EPA) per day has been shown to have potential antithrombotic effects, including an increased bleeding time and International Normalized Ratio (INR). Administration of omega-3 fatty acids should be avoided in patients taking anticoagulants and in those known to have an inherited or acquired predisposition to bleeding.

ADVERSE REACTIONS

Allergic sensitization has been reported following both oral and parenteral administration of folic acid.

You should call your doctor for medical advice about serious adverse events. To report adverse side effects or to obtain product information, contact CarWin Pharmaceutical Associates, LLC at 1-985-288-5122

DIRECTIONS

Adults

Take one softgel daily with or without food, or as prescribed by a healthcare practitioner.

Children under 12

Consult a doctor.

Do not exceed the recommended dose.

HOW SUPPLIED

TriStart DHA™ is available as oval, brown softgel capsules with a yellow imprint "TriStart". They are available in child-resistant bottles containing 30 softgels (15370-250-30) and in a 3ct professional sample (15370-250-03).

STORAGE AND HANDLING

Store at 20°-25°C (68°-77°F); excursions permitted to 15°-30°C (59°-86°F) [See USP Controlled Room Temperature.]

TriStart DHA™ should be administered only under the direct supervision of a healthcare practitioner.

Avoid excessive heat, light and moisture.

Keep out of reach of children.

Tamper Evident

Do not use if seal is broken or missing.

Manufactured for:
CarWin Pharmaceutical Associates, LLC
Slidell, LA 70461

Rx
MADE IN CANADA

Rev. 05/2015

PRINCIPAL DISPLAY PANEL - 30 Capsule Bottle Label

15370-250-30

TriStart
DHA
PRENATAL SUPPLEMENT

Dye Free, Lactose, Gluten
and Sugar Free

Rx
30 Softgels